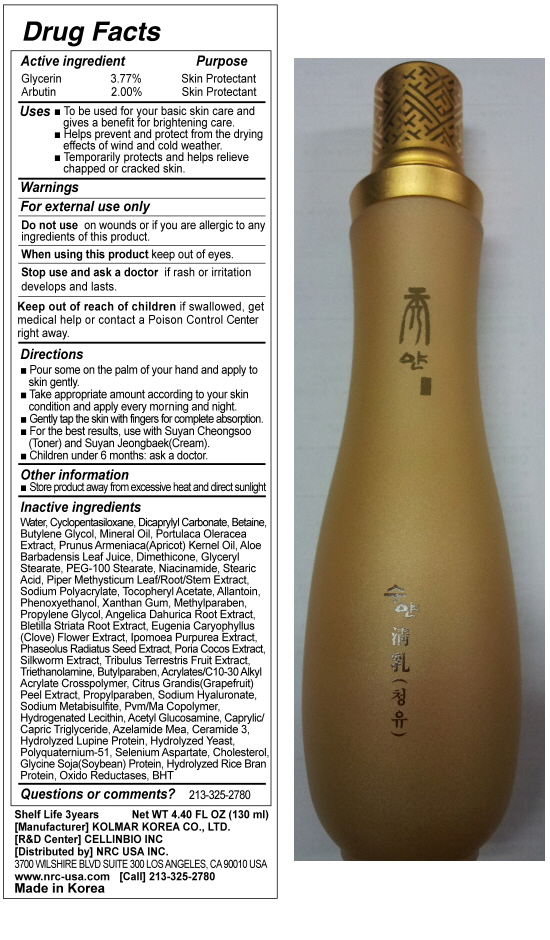 DRUG LABEL: SUYAN CHUNGSYU
NDC: 76173-1006 | Form: EMULSION
Manufacturer: Cellinbio Co Ltd
Category: otc | Type: HUMAN OTC DRUG LABEL
Date: 20111108

ACTIVE INGREDIENTS: GLYCERIN 4.9 mL/130 mL; ARBUTIN 2.6 mL/130 mL
INACTIVE INGREDIENTS: WATER; CYCLOMETHICONE 5; DICAPRYLYL CARBONATE; BETAINE; BUTYLENE GLYCOL; MINERAL OIL; PORTULACA OLERACEA WHOLE; APRICOT KERNEL OIL; ALOE VERA LEAF; DIMETHICONE; GLYCERYL MONOSTEARATE; PEG-100 STEARATE; NIACINAMIDE; STEARIC ACID; PIPER METHYSTICUM WHOLE; SODIUM POLYACRYLATE (8000 MW); ALPHA-TOCOPHEROL ACETATE; ALLANTOIN; PHENOXYETHANOL; XANTHAN GUM; METHYLPARABEN; PROPYLENE GLYCOL; ANGELICA DAHURICA ROOT; BLETILLA STRIATA BULB; CLOVE; IPOMOEA PURPUREA TOP; MUNG BEAN; FU LING; TRIBULUS TERRESTRIS FRUIT; TROLAMINE; BUTYLPARABEN; CITRUS MAXIMA FRUIT RIND; PROPYLPARABEN; HYALURONATE SODIUM; SODIUM METABISULFITE; MALEIC ANHYDRIDE; HYDROGENATED SOYBEAN LECITHIN; MEDIUM-CHAIN TRIGLYCERIDES; CERAMIDE 3; YEAST; CHOLESTEROL; SOY PROTEIN; RICE BRAN; BUTYLATED HYDROXYTOLUENE

SUYAN CHUNGYU

Drug Facts

Active Ingrdient
Glycerin 3.77%
Arbutin 2.00%

Purpose

Skin Protectant

Keep out of Reach of Children

If swallowed, get medical help or contact a Posion Control Center right away.

Indication & Usage

Directions
■ Pour some on the palm of your hand and apply to skin gently.
■ Take appropriate amount according to your skin condition and apply every morning and night.
■ Gently tap the skin with fingers for complete absorption.
■ For the best results, use with Suyan Cheongsoo(Toner) and Suyan Jeongbaek(Cream).
■ Children under 6 months: ask a doctor.

Warnings

For external use only
Do not use on wounds or if you are allergic to any ingredients of this product.
When using this product keep out of eyes.
Stop use and ask a doctor if rash or irritation develops and lasts.

Dosage & Administration

■ To be used for your basic skin care and gives a benefit for brightening care.
■ Helps prevent and protect from the drying effects of wind and cold weather.
■ Temporarily protects and helps relieve chapped or cracked skin.

SUYAN CHUNGYU

Water, Cyclopentasiloxane, Dicaprylyl Carbonate, Betaine, Butylene Glycol, Mineral Oil, Portulaca Oleracea Extract, Prunus Armeniaca(Apricot) Kernel Oil, Aloe Barbadensis Leaf Juice, Dimethicone, Glyceryl Stearate, PEG-100 Stearate, Niacinamide, Stearic Acid, Piper Methysticum Leaf/Root/Stem Extract, Sodium Polyacrylate, Tocopheryl Acetate, Allantoin, Phenoxyethanol, Xanthan Gum, Methylparaben, Propylene Glycol, Angelica Dahurica Root Extract, Bletilla Striata Root Extract, Eugenia Caryophyllus(Clove) Flower Extract, Ipomoea Purpurea Extract, Phaseolus Radiatus Seed Extract, Poria Cocos Extract, Silkworm Extract, Tribulus Terrestris Fruit Extract, Triethanolamine, Butylparaben, Acrylates/C10-30 Alkyl Acrylate Crosspolymer, Citrus Grandis(Grapefruit) Peel Extract, Propylparaben, Sodium Hyaluronate, Sodium Metabisulfite, Pvm/Ma Copolymer, Hydrogenated Lecithin, Acetyl Glucosamine, Caprylic/Capric Triglyceride, Azelamide Mea, Ceramide 3, Hydrolyzed Lupine Protein, Hydrolyzed Yeast, Polyquaternium-51, Selenium Aspartate, Cholesterol, Glycine Soja(Soybean) Protein, Hydrolyzed Rice Bran Protein, Oxido Reductases, BHT

SUYAN CHUNGYU

SUYAN CHEONGYU
Net WT. 4.40FL OZ(130ml)